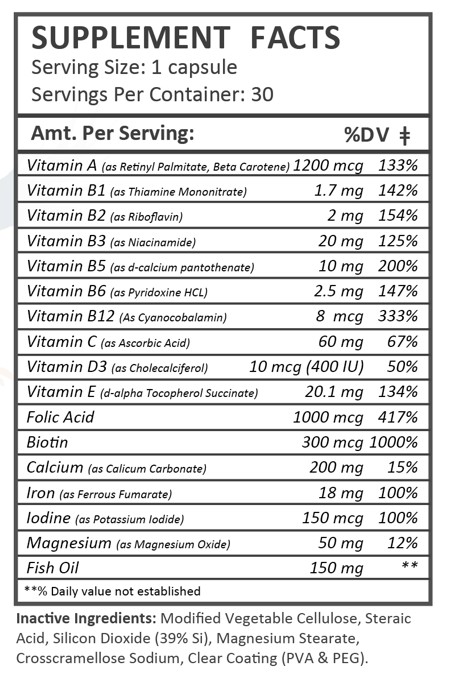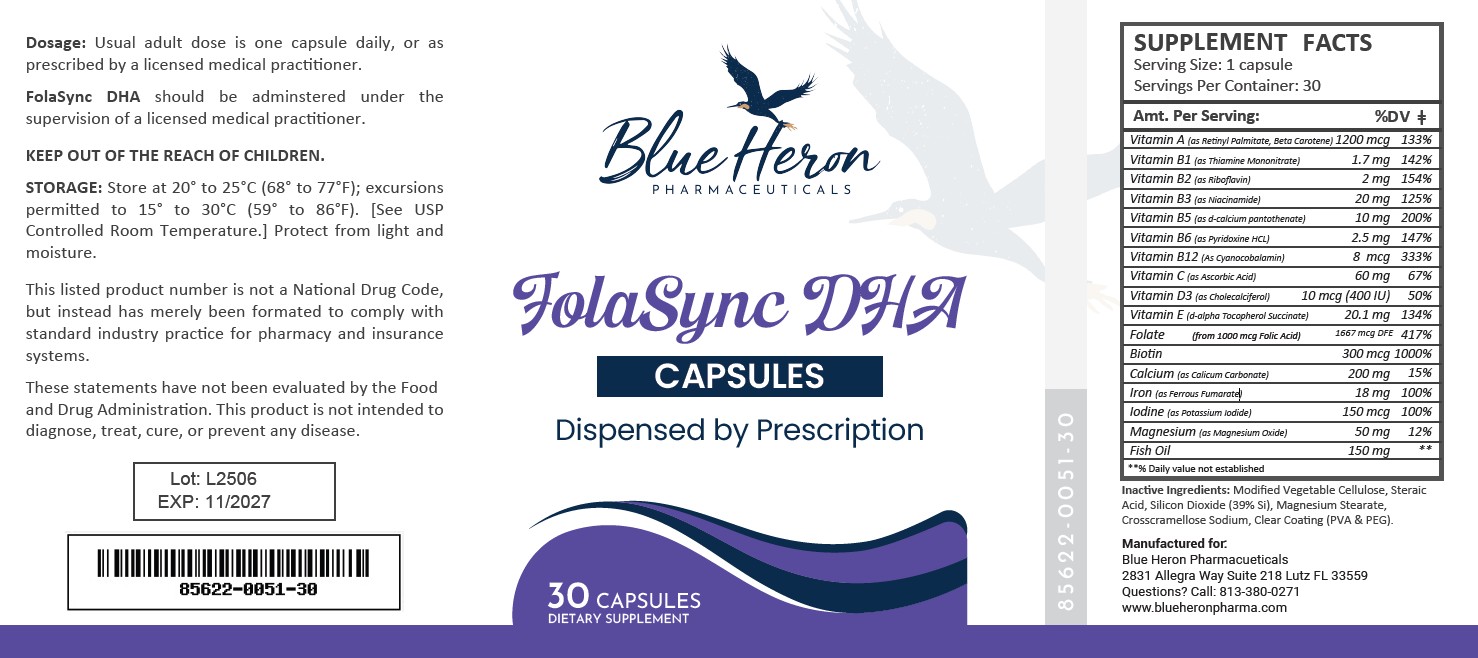 DRUG LABEL: FolaSync DHA
NDC: 85622-051 | Form: CAPSULE, GELATIN COATED
Manufacturer: Blue Heron Pharmaceuticals, LLC
Category: other | Type: DIETARY SUPPLEMENT
Date: 20260112

ACTIVE INGREDIENTS: BETA CAROTENE 600 ug/1 1; Vitamin A Palmitate 600 ug/1 1; Ascorbic Acid 60 mg/1 1; Cholecalciferol 10 ug/1 1; .ALPHA.-TOCOPHEROL, D- 20.1 mg/1 1; THIAMINE MONONITRATE 1.7 mg/1 1; Riboflavin 2 mg/1 1; Niacinamide 20 mg/1 1; Pyridoxine Hydrochloride 2.5 mg/1 1; Folic Acid 1000 ug/1 1; Cyanocobalamin 8 ug/1 1; Biotin 300 ug/1 1; Calcium Pantothenate 10 mg/1 1; Calcium Carbonate 200 mg/1 1; Iron 18 mg/1 1; Potassium Iodide 150 ug/1 1; Magnesium Oxide 50 mg/1 1; Fish Oil 150 mg/1 1

FolaSync DHA

Health Claim:

FolaSync DHA

Description:

FolaSync DHA Capsules are clear capsules dispensed in plastic bottles of 30 ct.

85622-0051-30

Reserved for Professional Recommendation

FolaSync DHA Capsules are an orally administered prescription vitamin to provide significant amounts of DHA, Vitamins B6, B12, C, D3, E, riboflavin, niacinamide, thiamine monoitrate, and folate to supplement the diet, and to help assure that nutritional deficiencies of these vitamines will not develop.

FolaSync DHA Capsules should be administered under the supervision of a licensed medical practitioner.

This listed product is not a National Drug Code, but instead has merely been formatted to comply with standard industry practice for pharmacy and insurance computer systems.

These statements have not been evaluated by the Food and Drug Administration. This product is not intended to diagnose, treat, cure or prevent any disease.

All prescriptions using this product shall be pursuant to state statutes as applicable. This is not an Orange Book product. This product may be administered only under a physician’s supervision. There are no implied or explicit claims on therapeutic equivalence.

Manufactured for:

Blue Heron Pharmaceuticals

Lutz, FL 33559

Warnings:

WARNING: Ingestion of more than 3 grams of omega-3 fatty acids (such as DHA) per day has been shown to have potential antithrombotic effects, including an increased bleeding time and International Normalized Ratio (INR). Administration of omega-3 fatty acids should be avoided in patients taking anticoagulants and in those known to have an inherited or acquired predisposition to bleeding.

WARNING: Accidental overdose of iron-containing products is a leading cause of fatal poisoning in children under 6. Keep this product out of reach of children. In case of accidental overdose, call a doctor or poison control center immediately.

This product is contraindicated in patients with a known hypersensitivity to any of the ingredients.

FolaSync DHA Capsules should only be used under the direction and supervision of a licensed medical practitioner. Use with caution in patients that may have a medical condition, are pregnant, lactating, trying to conceive, under the age of 18, or taking medications.

These statements have not been evaluated by the Food and Drug Administration. This product is not intended to diagnose, treat, cure, or prevent any disease.

Precautions:

CONTRAINDICATIONS
This product is contraindicated in patients with known hypersensitivity to any of the ingredients.

PRECAUTIONS
This product is contraindicated in patients with a known hypersensitivity to any of the ingredients.

ADVERSE REACTIONS
Allergic sensitizations have been reported following oral administration of folic acid. Consult your physician immediately if adverse side effects occur.

KEEP OUT OF THE REACH OF CHILDREN.

Dosage and Administration:

Usual adult dose is 1 capsule by mouth daily once daily, or as prescribed by a licensed medical practitioner.

Storage:

Store at 20° to 25°C (68° to 77°F); excursions permitted to 15° to 30°C (59° to 86°F). [See USP Controlled Room Temperature.] Protect from light and moisture.